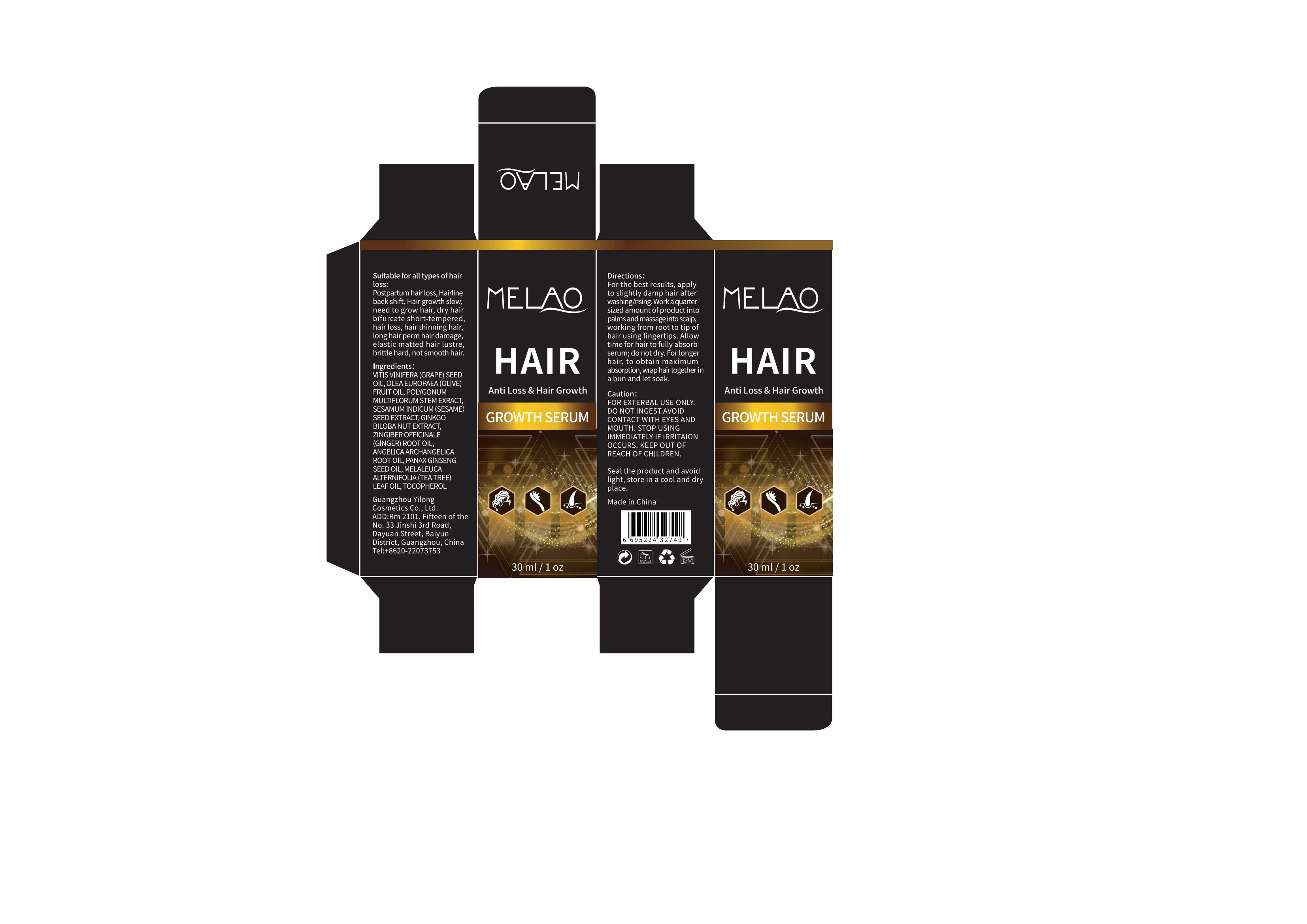 DRUG LABEL: MELAO Hair Growth Serum
NDC: 83566-144 | Form: LIQUID
Manufacturer: Guangdong Aimu Biological Technology Co., Ltd
Category: otc | Type: HUMAN OTC DRUG LABEL
Date: 20240623

ACTIVE INGREDIENTS: SESAMUM INDICUM WHOLE 2 g/100 mL; POLYGONUM BISTORTA ROOT 2 g/100 mL; ZINGIBER OFFICINALE WHOLE 1 g/100 mL; PANAX GINSENG ROOT OIL 0.5 g/100 mL
INACTIVE INGREDIENTS: TOCOPHEROL; GINKGO BILOBA WHOLE; VITIS VINIFERA SEED; OLEA EUROPAEA FRUIT VOLATILE OIL; ANGELICA ARCHANGELICA ROOT

Active ingredients

POLYGONUM MULTIFLORUM STEM EXRACT 2%
SESAMUM INDICUM（SESAME）SEED EXTRACT 2%

ZINGIBER OFFICINALE (GINGER) ROOT OIL 1%

PANAX GINSENG SEED OIL 0.5%

Purpose

Hair growth

Uses

apply to slightly damp hair after washing/rising.

Work a quarter sized amount of product into palms and massage into scalp, working from root to tip of hair using fingertips.

Warnings

For external use only.

Stop use and ask a doctor if

rash occurs.

Do not use

on damaged or broken skin.

When using this product

keep out of eyes. Rinse with water to remove.

Keep out of reach of children.

If swallowed, get medical help or contact a Poison Control Center right away.

Dosage

Work a quarter sized amount of product into palms and massage into scalp, working from root to tip of hair using fingertips.

Inactive ingredients

VITIS VINIFERA (GRAPE) SEED OIL 57.5%
OLEA EUROPAEA (OLIVE) FRUIT OIL 30%

GINKGO BILOBA NUT EXTRACT 1%

ANGELICA ARCHANGELICA ROOT OIL 1.5%

MENTHA HAPLOCALYX OIL 3%
TOCOPHEROL 1.5%